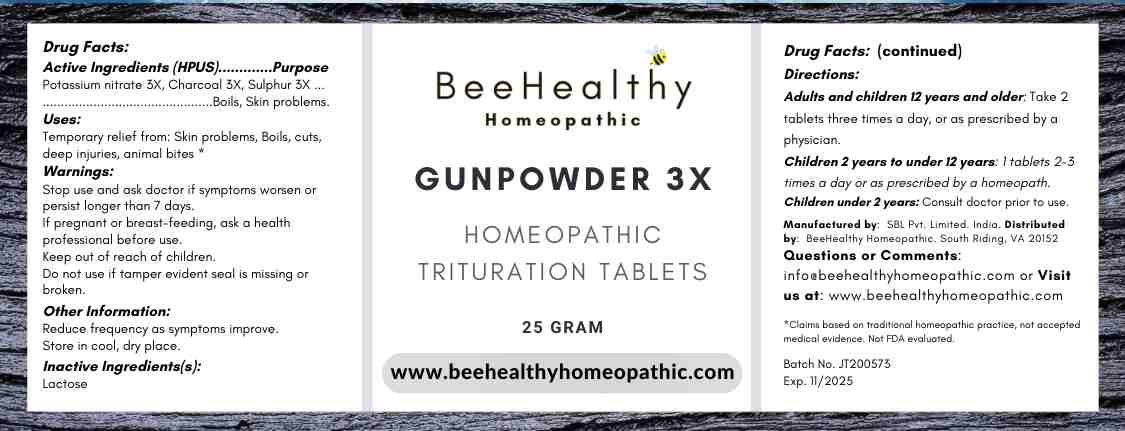 DRUG LABEL: Gun Powder
NDC: 79718-0061 | Form: TABLET
Manufacturer: Warsan Homeopathic
Category: homeopathic | Type: HUMAN OTC DRUG LABEL
Date: 20201211

ACTIVE INGREDIENTS: POTASSIUM NITRATE 3 [hp_X]/1 1; ACTIVATED CHARCOAL 3 [hp_X]/1 1; SULFUR 3 [hp_X]/1 1
INACTIVE INGREDIENTS: LACTOSE MONOHYDRATE

ACTIVE INGREDIENT

Potassium Nitrate 3X, Charcoal 3X, Sulphur 3X

INACTIVE INGREDIENT

Lactose

Stop use and ask doctor if symptoms worsen or persist longer than 7 days.

Do not use if tamper evident seal is missing or broken.

INDICATIONS AND USAGE

Temporary relief from skin problems, boils, cuts, deep injuries, animal bites

PURPOSE

Temporary relief of skin problems, boils, cuts, deep injuries, animal bites

DOSAGE AND ADMINISTRATION

Adults and children 12 years of age and older: Take 2 talbets three times a day or as prescribed by doctor.

Children 2 years to 12 years of age: Take 1-2 tablets two to three time pers day or as prescribed by doctor.

Children under 2 years of age: Consult doctor prior to use.

Keep out of reach of children.